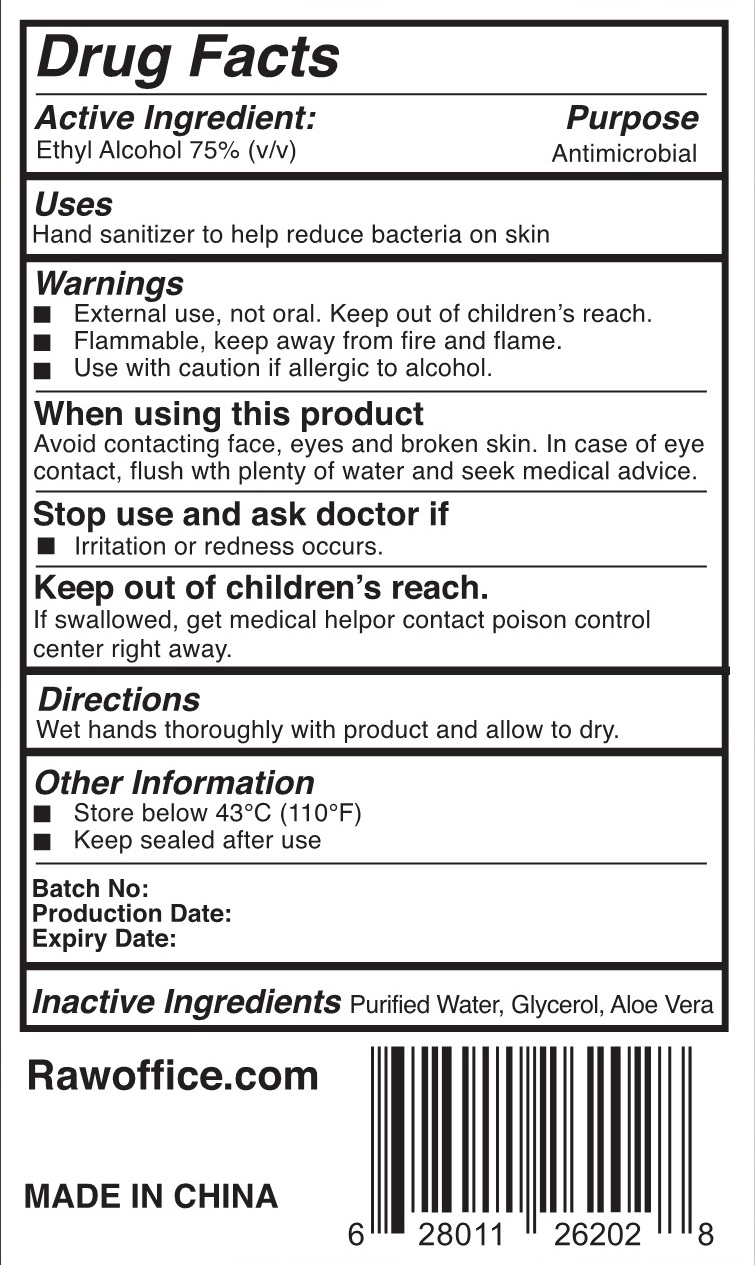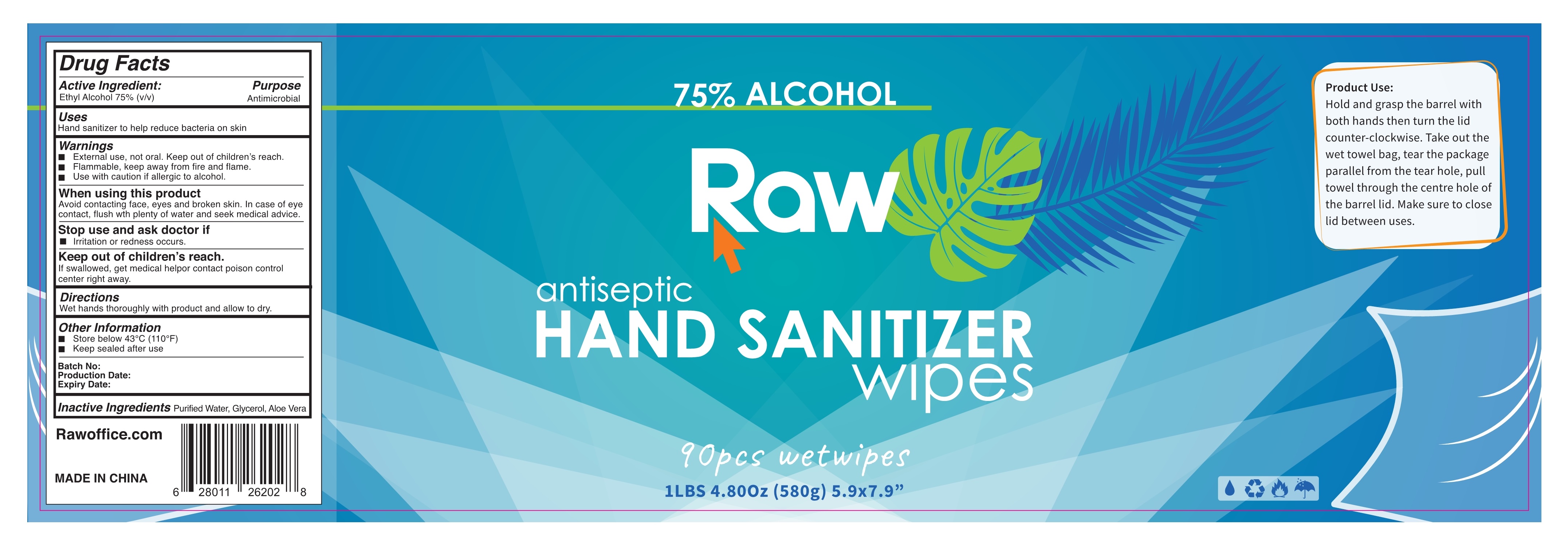 DRUG LABEL: RAW ANTISEPTIC HAND SANITIZER WIPES
NDC: 75163-090 | Form: CLOTH
Manufacturer: Zhuji Jianhe Paper Co., Ltd
Category: otc | Type: HUMAN OTC DRUG LABEL
Date: 20200902

ACTIVE INGREDIENTS: ALCOHOL 75 mL/100 mL
INACTIVE INGREDIENTS: GLYCERIN; ALOE VERA LEAF; WATER

75163-090 jianhe 90 cloth RAW ANTISEPTIC HAND SANITIZER WIPES / ethyl alcohol

Active Ingredient(s)

Ethyl Alcohol 75% v/v. Purpose: Antimicrobial

Purpose

Antimicrobial.

Use

Hand sanitizer to help reduce bacteria on skin

Warnings

■ External use, not oral. Keep out of children's reach.

■ Flammable, keep away from fire and flame.

■ Use with caution if allergic to alcohol.

When using this product

Avoid contacting face, eyes and broken skin. In case of eye contact, flush with plenty of water and seek medical advice.

Stop use and ask doctor if

■ Irritation or redness occurs.

Keep out of reach of children.If swallowed, get medical help or contact poison control center right away.

Directions

Wet hands thoroughly with product and allow to dry.

Inactive ingredients

Purified Water, Glycerol, Aloe Vera

Do not use

on children less than 2 months of age
on open skin wounds

Other information

■ Store below 43°C (110°F)

■ Keep sealed after use

SPL UNCLASSIFIED SECTION

Product Use:

Hold and grasp the barrel with both hands then turn the lid counter-clockwise. Take out the wet towel bag, tear the package parallel from the tear hole, pull towel through the centre hole of the barrel lid. Make sure to close lid between uses.

Rawoffice.com

MADE IN CHINA

Package Label - Principal Display Panel

90 pcs wetwipes NDC:75163-090-01